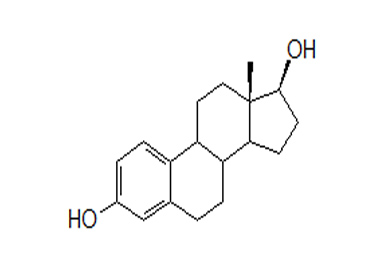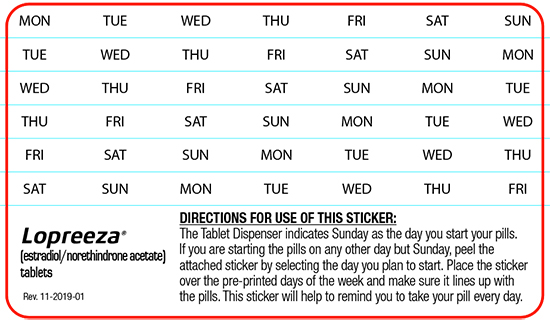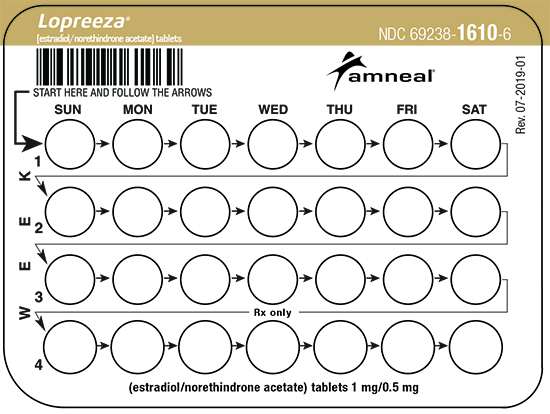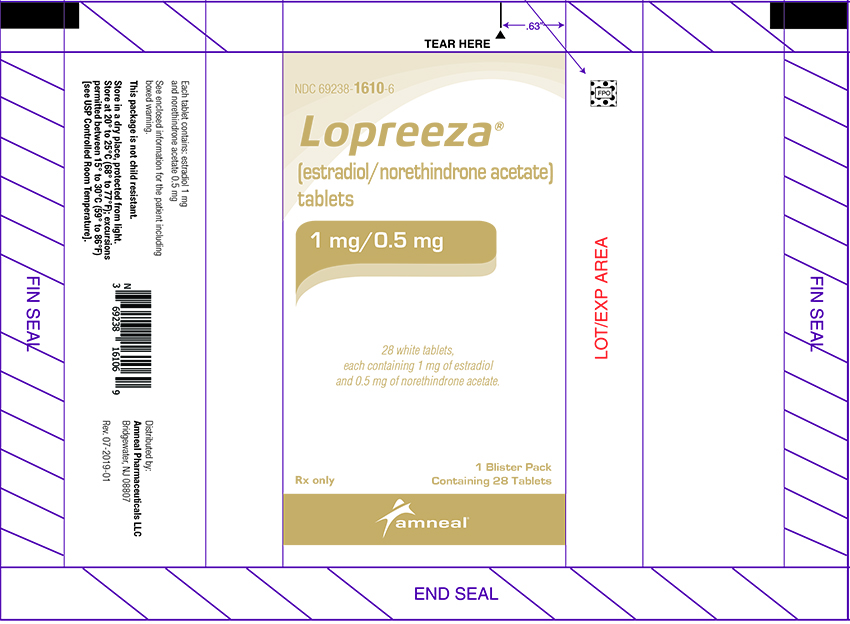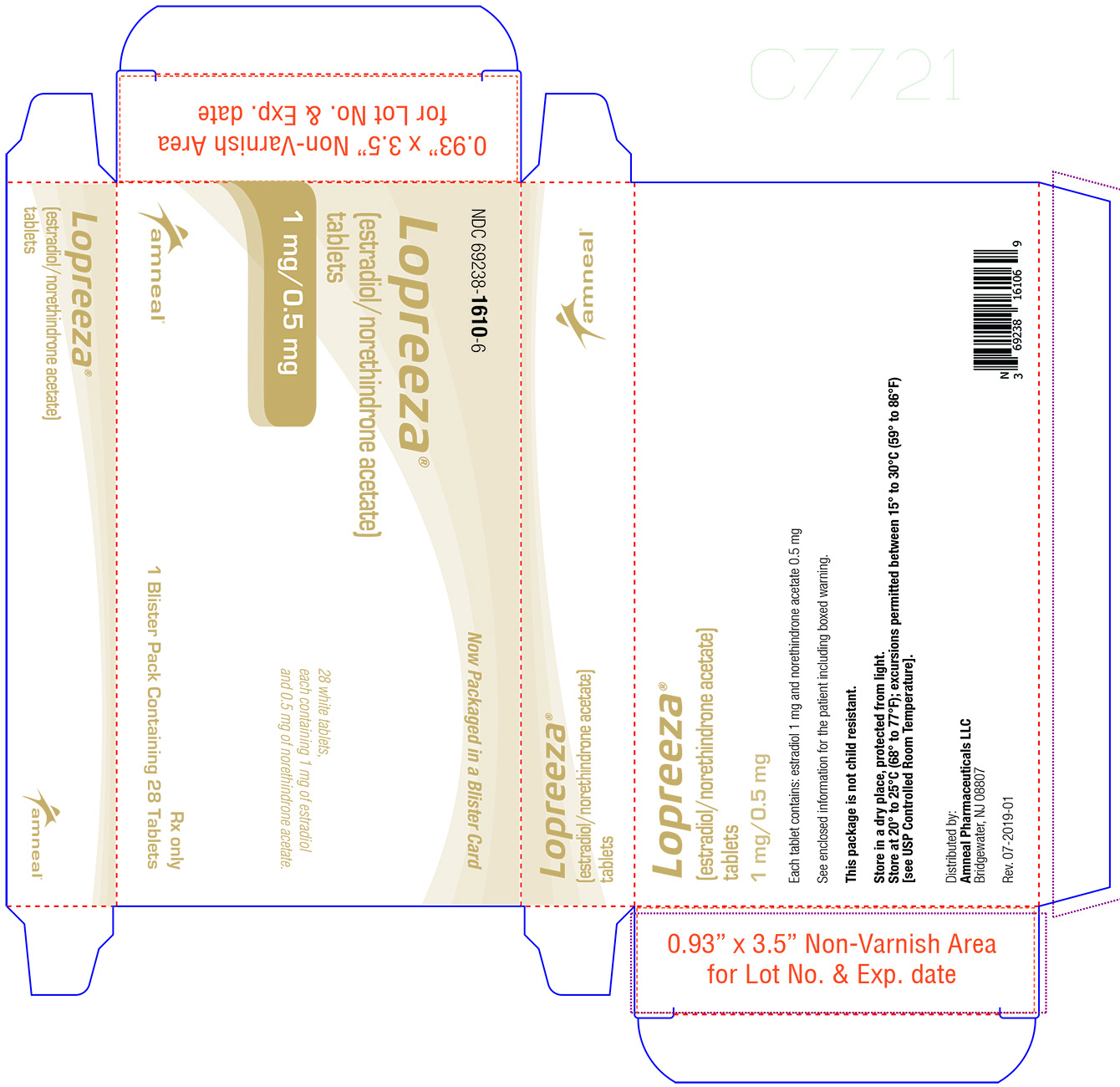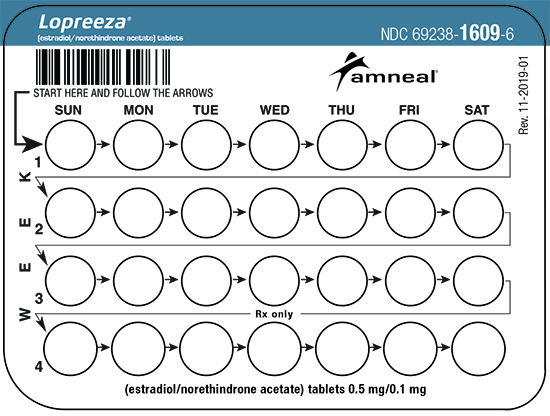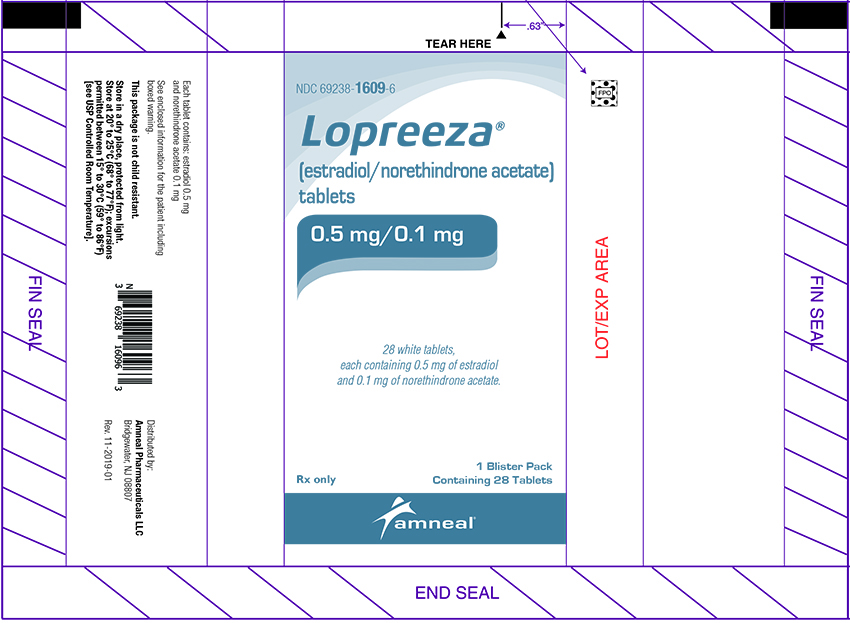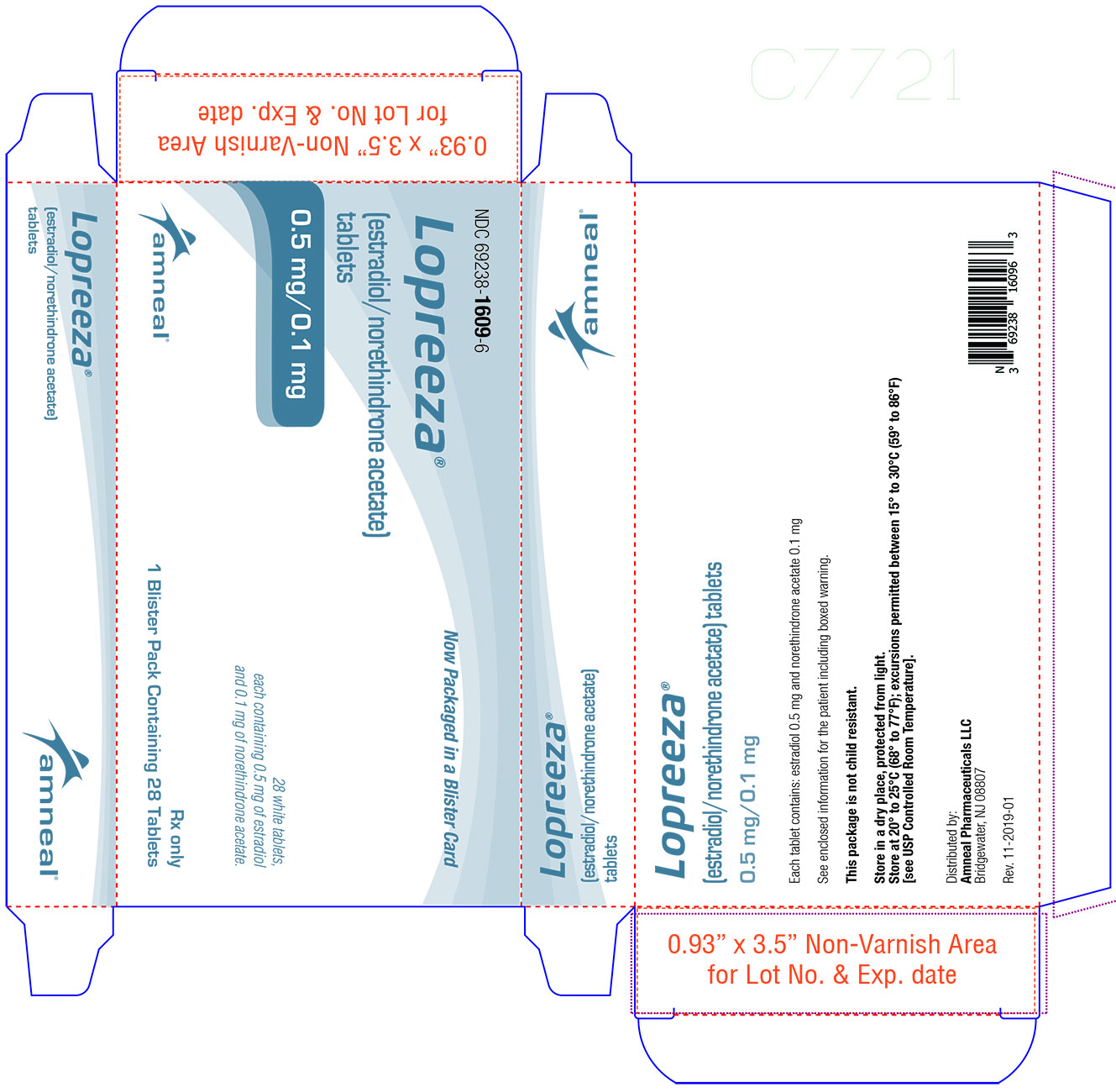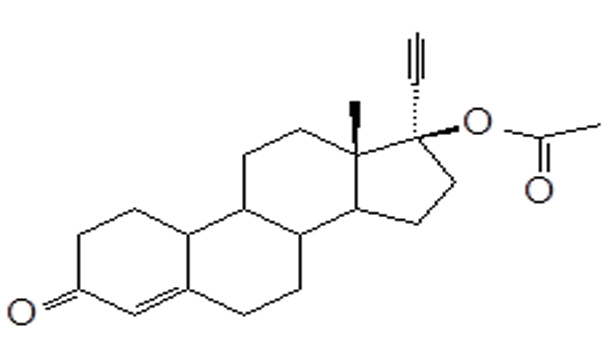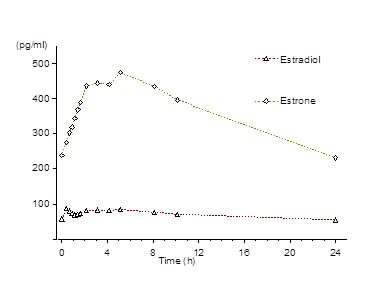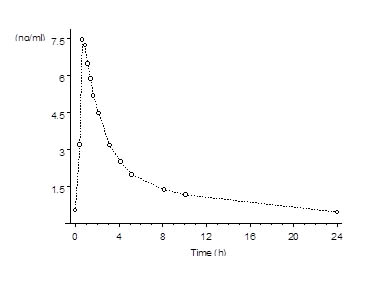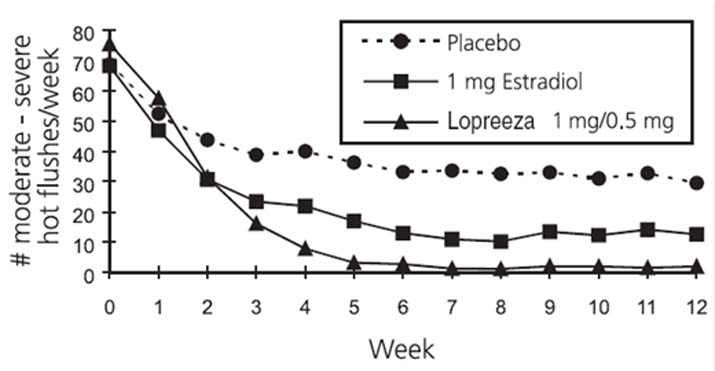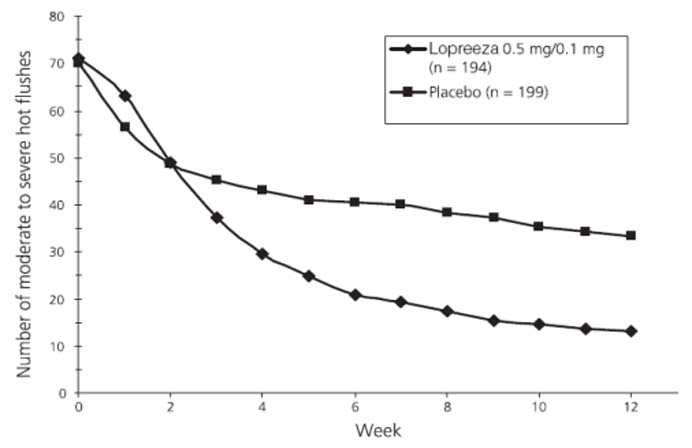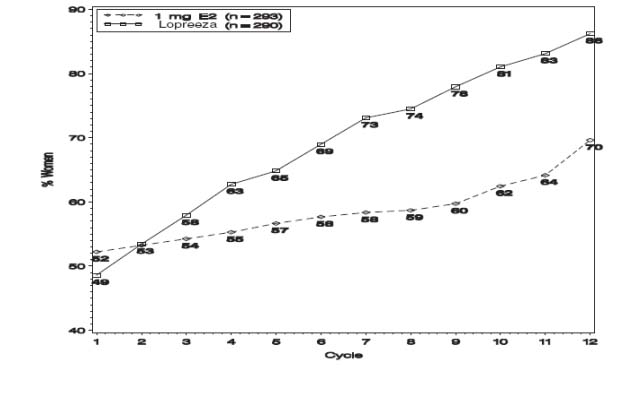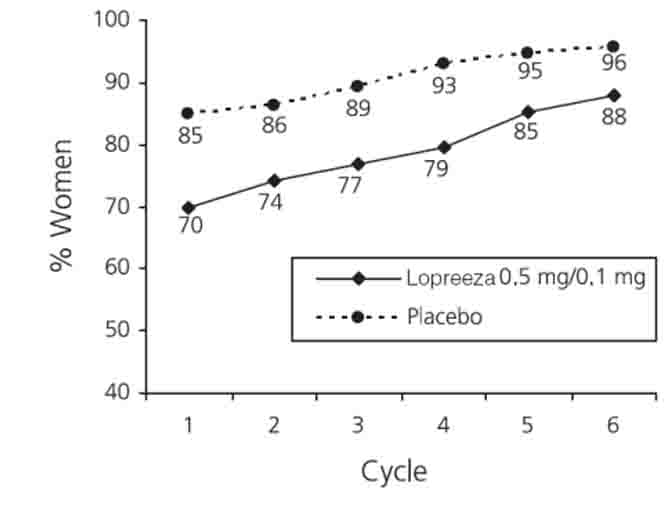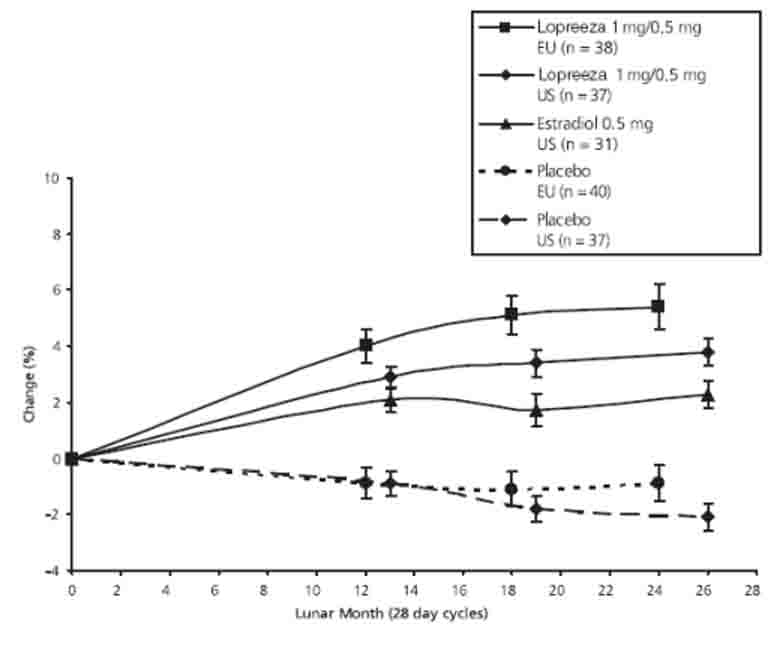 DRUG LABEL: LOPREEZA
NDC: 69238-1610 | Form: TABLET, FILM COATED
Manufacturer: Amneal Pharmaceuticals NY LLC
Category: prescription | Type: HUMAN PRESCRIPTION DRUG LABEL
Date: 20250116

ACTIVE INGREDIENTS: ESTRADIOL 1 mg/1 1; NORETHINDRONE ACETATE 0.5 mg/1 1
INACTIVE INGREDIENTS: LACTOSE MONOHYDRATE; STARCH, CORN; COPOVIDONE K25-31; TALC; MAGNESIUM STEARATE; HYPROMELLOSES; TRIACETIN

HIGHLIGHTS OF PRESCRIBING INFORMATION

These highlights do not include all the information needed to use LOPREEZA safely and effectively. See full prescribing information for LOPREEZA.
LOPREEZA® (estradiol/norethindrone acetate) tablets, for oral use
Initial U.S. Approval: 1998

WARNING: CARDIOVASCULAR DISORDERS, PROBABLE DEMENTIA, BREAST CANCER, and ENDOMETRIAL CANCER

See full prescribing information for complete boxed warning

Estrogen Plus Progestin Therapy

- The Women’s Health Initiative (WHI) estrogen plus progestin substudy reported increased risks of deep vein thrombosis (DVT), pulmonary embolism (PE), stroke and myocardial infarction (MI) (5.1)
- The WHI estrogen plus progestin substudy reported increased risks of invasive breast cancer (5.2)
- The WHI Memory Study (WHIMS) estrogen plus progestin ancillary study of WHI reported an increased risk of probable dementia in postmenopausal women 65 years of age and older (5.3)
- Do not use estrogen plus progestogen therapy for the prevention of cardiovascular disease or dementia (5.1, 5.3)
  Estrogen-Alone Therapy
- There is an increased risk of endometrial cancer in a woman with a uterus who use unopposed estrogens (5.2)
- The WHI estrogen-alone substudy reported increased risks of stroke and DVT (5.1)
- The WHIMS estrogen-alone ancillary study of WHI reported an increased risk of probable dementia in postmenopausal women 65 years of age and older (5.3)
- Do not use estrogen-alone therapy for the prevention of cardiovascular disease or dementia (5.2, 5.3)

1 INDICATIONS AND USAGE

Lopreeza is an estrogen and progestin combination indicated in a woman with a uterus for:

- Treatment of Moderate to Severe Vasomotor Symptoms due to Menopause (1.1)
- Treatment of Moderate to Severe Symptoms of Vulvar and Vaginal Atrophy due to Menopause (1.2)
  Limitations of Use:
  When prescribing solely for the treatment of moderate to severe symptoms of vulvar and vaginal atrophy due to menopause, first consider the use of topical vaginal products.
- Prevention of Postmenopausal Osteoporosis (1.3)

Limitations of Use:

When prescribing solely for the prevention of postmenopausal osteoporosis, first consider the use of non-estrogen medications. Consider estrogen therapy only for women at significant risk of osteoporosis.

2 DOSAGE AND ADMINISTRATION

- Take a single Lopreeza 1 mg/0.5 mg or 0.5 mg/0.1 mg tablet orally once daily for the Treatment of Moderate to severe Vasomotor Symptoms due to Menopause and for the Prevention of Postmenopausal Osteoporosis (2.1, 2.3)
- Lopreeza 1 mg/0.5 mg tablets are taken orally once daily for the Treatment of Moderate to Severe Symptoms of Vulvar and Vaginal Atrophy due to Menopause (2.2)

3 DOSAGE FORMS AND STRENGTHS

- Lopreeza (estradiol/norethindrone acetate) 1 mg/0.5 mg tablet (3)
- Lopreeza (estradiol/norethindrone acetate) 0.5 mg/0.1 mg tablet (3)

4 CONTRAINDICATIONS

- Undiagnosed abnormal genital bleeding (4)
- Breast cancer or a history of breast cancer (4, 5.2)

- Estrogen-dependent neoplasia (4, 5.2)

- Active DVT, PE, or history of these conditions (4, 5.1)

- Active arterial thromboembolic disease (for example, stroke and MI), or a history of these conditions (4, 5.1)

- Known anaphylactic reaction, angioedema, or hypersensitivity to Lopreeza (4)

- Hepatic impairment or disease (4, 5.10)
- Protein C, protein S, or antithrombin deficiency, or other known thrombophilic disorders (4)

5 WARNINGS AND PRECAUTIONS

- Estrogens increase the risk of gall bladder disease (5.4)
- Discontinue estrogen if severe hypercalcemia, loss of vision, severe hypertriglyceridemia or cholestatic jaundice occurs (5.5, 5.6, 5.9, 5.10)
- Monitor thyroid function in women on thyroid replacement therapy (5.11, 5.18)

6 ADVERSE REACTIONS

The most common adverse reactions (incidence ≥ 5 percent) with Lopreeza are: back pain, headache, pain in the extremity, nausea, diarrhea, gastroenteritis, insomnia, emotional lability, upper respiratory tract infection, sinusitis, nasopharyngitis, weight increase, breast pain, post-menopausal bleeding, uterine fibroid vaginal hemorrhage, ovarian cyst, endometrial thickening, viral infection, moniliasis genital, and accidental injury. (6.1)

To report SUSPECTED ADVERSE REACTIONS, contact Amneal Pharmaceuticals at 1-877-835-5472 or FDA at 1-800-FDA-1088 or www.fda.gov/medwatch.

7 DRUG INTERACTIONS

- Inducers and/or inhibitors of CYP3A4 may affect estrogen drug metabolism and decrease or increase the estrogen plasma concentration. (7)

FULL PRESCRIBING INFORMATION

WARNING: CARDIOVASCULAR DISORDERS, PROBABLE DEMENTIA, BREAST CANCER, and ENDOMETRIAL CANCER

Estrogen Plus Progestin Therapy

Cardiovascular Disorders and Probable Dementia

The Women’s Health Initiative (WHI) estrogen plus progestin substudy reported increased risks of deep vein thrombosis (DVT), pulmonary embolism (PE), stroke and myocardial infarction (MI) in postmenopausal women (50 to 79 years of age) during 5.6 years of treatment with daily oral conjugated estrogen (CE) [0.625 mg] combined with medroxyprogesterone acetate (MPA) [2.5 mg], relative to placebo [see Warnings and Precautions (5.1), and Clinical Studies (14.5)].

The WHI Memory Study (WHIMS) estrogen plus progestin ancillary study of the WHI reported an increased risk of developing probable dementia in postmenopausal women 65 years of age and older during 4 years of treatment with daily CE (0.625 mg) combined with MPA (2.5 mg), relative to placebo. It is unknown whether this finding applies to younger postmenopausal women [see Warnings and Precautions (5.3), Use in Specific Populations (8.5), and Clinical Studies (14.6)].

Do not use estrogen plus progestogen therapy for the prevention of cardiovascular disease or dementia [see Warnings and Precautions (5.1, 5.3), and Clinical Studies (14.5, 14.6)].

Breast Cancer

The WHI estrogen plus progestin substudy also demonstrated an increased risk of invasive breast cancer [see Warnings and Precautions (5.2), and Clinical Studies (14.5)].

Only daily oral 0.625 mg CE and 2.5 mg MPA were studied in the estrogen plus progestin substudy of the WHI. Therefore, the relevance of the WHI findings regarding adverse cardiovascular events, dementia and breast cancer to lower CE plus other MPA doses, other routes of administration, or other estrogen plus progestogen products is not known. Without such data, it is not possible to definitively exclude these risks or determine the extent of these risks for other products. Discuss with your patient the benefits and risks of estrogen plus progestogen therapy, taking into account her individual risk profile.

Prescribe estrogens with or without progestogens at the lowest effective doses and for the shortest duration consistent with treatment goals and risks for the individual woman.

Estrogen-Alone Therapy

Endometrial Cancer

There is an increased risk of endometrial cancer in a woman with a uterus who uses unopposed estrogens. Adding a progestogen to estrogen therapy has been shown to reduce the risk of endometrial hyperplasia, which may be a precursor to endometrial cancer. Adequate diagnostic measures, including directed or random endometrial sampling when indicated, should be undertaken to rule out malignancy in postmenopausal women with undiagnosed persistent or recurring abnormal genital bleeding [see Warnings and Precautions (5.2)].

Cardiovascular Disorders and Probable Dementia

The WHI estrogen-alone substudy reported increased risks of stroke and DVT in postmenopausal women (50 to 79 years of age) during 7.1 years of treatment with daily oral CE (0.625 mg)-alone, relative to placebo [see Warnings and Precautions (5.1), and Clinical Studies (14.5)].

The WHIMS estrogen-alone ancillary study of the WHI reported an increased risk of developing probable dementia in postmenopausal women 65 years of age and older during 5.2 years of treatment with daily CE (0.625 mg)-alone, relative to placebo. It is unknown whether this finding applies to younger postmenopausal women [see Warnings and Precautions (5.3), Use in Specific Populations (8.5), and Clinical Studies (14.6)].

Do not use estrogen-alone therapy for the prevention of cardiovascular disease or dementia [see Warnings and Precautions (5.1, 5.3), and Clinical Studies (14.5, 14.6)].

Only daily oral 0.625 mg CE was studied in the estrogen-alone substudy of the WHI. Therefore, the relevance of the WHI findings regarding adverse cardiovascular events and dementia to lower CE doses, other routes of administration, or other estrogen-alone products is not known. Without such data, it is not possible to definitively exclude these risks or determine the extent of these risks for other products. Discuss with your patient the benefits and risks of estrogen-alone therapy, taking into account her individual risk profile.

Prescribe estrogens with or without progestogens at the lowest effective doses and for the shortest duration consistent with treatment goals and risks for the individual woman.

1 INDICATIONS AND USAGE

Lopreeza is indicated for:

1.2 Treatment of Moderate to Severe Symptoms of Vulvar and Vaginal Atrophy due to Menopause

Limitation of Use

When prescribing solely for the treatment of moderate to severe symptoms of vulvar and vaginal atrophy due to menopause, first consider the use of topical vaginal products.

1.3 Prevention of Postmenopausal Osteoporosis

Limitation of Use

When prescribing solely for the prevention of postmenopausal osteoporosis, first consider the use of non-estrogen medications. Consider estrogen therapy only for women at significant risk of osteoporosis.

2 DOSAGE AND ADMINISTRATION

Use estrogen-alone, or in combination with a progestogen, at the lowest effective dose and the shortest duration consistent with treatment goals and risks for the individual woman. Reevaluate postmenopausal women periodically as clinically appropriate to determine whether treatment is still necessary.

2.1 Treatment of Moderate to Severe Vasomotor Symptoms due to Menopause

Take a single Lopreeza tablet orally once daily for the treatment of moderate to severe vasomotor symptoms due to menopause.

- Lopreeza 1 mg/0.5 mg
- Lopreeza 0.5 mg/0.1 mg

2.2 Treatment of Moderate to Severe Symptoms of Vulvar and Vaginal Atrophy due to Menopause

Take a single Lopreeza tablet orally once daily for the treatment of moderate to severe symptoms of vulvar and vaginal atrophy due to menopause.

- Lopreeza 1 mg/0.5 mg

2.3 Prevention of Postmenopausal Osteoporosis

Take a single Lopreeza tablet orally once daily for the prevention of postmenopausal osteoporosis.

- Lopreeza 1 mg/0.5 mg
- Lopreeza 0.5 mg/0.1 mg

3 DOSAGE FORMS AND STRENGTHS

Lopreeza is available in two strengths:

- Lopreeza 1 mg/ 0.5 mg contains 1 mg of estradiol and 0.5 mg of norethindrone acetate. The tablets are white, round, biconvex, film-coated tablets debossed with “ALH” on the one side and plain on the other side.

- Lopreeza 0.5 mg/ 0.1 mg contains 0.5 mg of estradiol and 0.1 mg of norethindrone acetate. The tablets are white, round, biconvex, film-coated tablets debossed with “ALL” on the one side and plain on the other side.

4 CONTRAINDICATIONS

Lopreeza is contraindicated in women with any of the following conditions:

- Undiagnosed abnormal genital bleeding [see Warnings and Precautions (5.2)]
- Breast cancer or history of breast cancer [see Warnings and Precautions (5.2)]
- Estrogen-dependent neoplasia [see Warnings and Precautions (5.2)]
- Active DVT, PE, or history of these conditions [see Warnings and Precautions (5.1)]
- Active arterial thromboembolic disease (for example, stroke and MI), or a history of these conditions [see Warnings and Precautions (5.1)]
- Known anaphylactic reaction, angioedema, or hypersensitivity to Lopreeza
- Hepatic impairment or disease
- Protein C, protein S, or antithrombin deficiency, or other known thrombophilic disorders

5 WARNINGS AND PRECAUTIONS

5.1 Cardiovascular Disorders

Increased risks of PE, DVT, stroke and MI are reported with estrogen plus progestin therapy. Increased risks of stroke and DVT are reported with estrogen-alone therapy. Immediately discontinue estrogen with or without progestogen therapy if any of these occur or is suspected.

Manage appropriately any risk factors for arterial vascular disease (for example, hypertension, diabetes mellitus, tobacco use, hypercholesterolemia, and obesity) and/or venous thromboembolism (VTE) (for example, personal history or family history of VTE, obesity, and systemic lupus erythematosus).

Stroke

The WHI estrogen plus progestin substudy reported a statistically significant increased risk of stroke in women 50 to 79 years of age receiving daily CE (0.625 mg) plus MPA (2.5 mg) compared to women in the same age group receiving placebo (33 versus 25 strokes per 10,000 women-years) [see Clinical Studies (14.5)]. The increase in risk was demonstrated after the first year and persisted.^1 Immediately discontinue estrogen with or without progestogen therapy if a stroke occurs or is suspected.

The WHI estrogen-alone substudy reported a statistically significant increased risk of stroke in women 50 to 79 years of age receiving daily CE (0.625 mg)-alone compared to women in the same age group receiving placebo (45 versus 33 strokes per 10,000 women-years, respectively). The increase in risk was demonstrated in year 1 and persisted [see Clinical Studies (14.5)]. Immediately discontinue estrogen-alone therapy if a stroke occurs or is suspected.

Subgroup analyses of women 50 to 59 years of age suggest no increased risk of stroke for those women receiving CE (0.625 mg)-alone versus those receiving placebo (18 versus 21 per 10,000 women-years).^1

Coronary Heart Disease

The WHI estrogen plus progestin substudy reported an increased risk (not statistically significant) of coronary heart disease (CHD) events (defined as nonfatal MI, silent MI, or CHD death) in those women receiving daily CE (0.625 mg) plus MPA (2.5 mg) compared to women receiving placebo (41 versus 34 per 10,000 women-years). ^1An increase in relative risk was demonstrated in year 1, and a trend toward decreasing relative risk was reported in years 2 through 5 [see Clinical Studies (14.5)].

The WHI estrogen-alone substudy reported no overall effect on CHD events in women receiving estrogen-alone compared to placebo ^2 [see Clinical Studies (14.5)].

Subgroup analyses of women 50 to 59 years of age, who were less than 10 years since menopause, suggest a reduction (not statistically significant) in CHD events in those women receiving daily CE (0.625 mg)-alone compared to placebo (8 versus 16 per 10,000 women-years).^1

In postmenopausal women with documented heart disease (n=2,763), average 66.7 years of age, in a controlled clinical trial of secondary prevention of cardiovascular disease (Heart and Estrogen/Progestin Replacement Study; HERS), treatment with daily CE (0.625 mg plus MPA (2.5 mg) demonstrated no cardiovascular benefit. During an average follow-up of 4.1 years, treatment with CE plus MPA did not reduce the overall rate of CHD events in postmenopausal women with established CHD. There were more CHD events in the CE plus MPA-treated group than in the placebo group in year 1, but not during the subsequent years. Two thousand three hundred twenty‑one (2,321) women from the original HERS trial agreed to participate in an open label extension of HERS, HERS II. Average follow-up in HERS II was an additional 2.7 years, for a total of 6.8 years overall. Rates of CHD events were comparable among women in the CE plus MPA group and the placebo group in HERS, HERS II, and overall.

Venous Thromboembolism

The WHI estrogen plus progestin substudy reported a statistically significant 2-fold greater rate of VTE (DVT and PE) in women receiving daily CE (0.625 mg) plus MPA (2.5 mg) compared to women receiving placebo (35 versus 17 per 10,000 women-years). Statistically significant increases in risk for both DVT (26 versus 13 per 10,000 women-years) and PE (18 versus 8 per 10,000 women-years) were also demonstrated. The increase in VTE risk was demonstrated during the first year and persisted ^3 [see Clinical Studies (14.5)]. Immediately discontinue estrogen plus progestogen therapy if a VTE occurs or is suspected.

In the WHI estrogen-alone substudy, the risk of VTE was increased for women receiving daily CE

(0.625 mg)-alone compared to placebo (30 versus 22 per 10,000 women-years), although only the increased risk of DVT reached statistical significance (23 versus 15 per 10,000 women-years). The increase in VTE risk was demonstrated during the first 2 years ^4 [see Clinical Studies (14.5)]. Immediately discontinue estrogen-alone therapy if a VTE occurs or is suspected.

If feasible, discontinue estrogens at least 4 to 6 weeks before surgery of the type associated with an increased risk of thromboembolism, or during periods of prolonged immobilization.

5.2 Malignant Neoplasms

Breast Cancer

After a mean follow-up of 5.6 years, the WHI substudy of daily CE (0.625 mg) plus MPA (2.5 mg) reported an increased risk of invasive breast cancer in women who took daily CE plus MPA compared to placebo.

In this substudy, prior use of estrogen-alone or estrogen plus progestin therapy was reported by 26 percent of the women. The relative risk of invasive breast cancer was 1.24, and the absolute risk was 41 versus 33 cases per 10,000 women-years, for CE plus MPA compared with placebo. Among women who reported prior use of hormone therapy, the relative risk of invasive breast cancer was 1.86, and the absolute risk was 46 versus 25 cases per 10,000 women-years, for CE plus MPA compared with placebo. Among women who reported no prior use of hormone therapy, the relative risk of invasive breast cancer was 1.09, and the absolute risk was 40 versus 36 cases per 10,000 women-years, for CE plus MPA compared with placebo. In the same substudy, invasive breast cancers were larger, were more likely to be node positive, and were diagnosed at a more advanced stage in the CE (0.625 mg) plus MPA (2.5 mg) group compared with the placebo group. Metastatic disease was rare, with no apparent difference between the two groups. Other prognostic factors, such as histologic subtype, grade and hormone receptor status did not differ between the groups ^5 [see Clinical Studies (14.5)].

The WHI substudy of daily CE (0.625 mg)-alone provided information about breast cancer in estrogen-alone users. In the WHI estrogen-alone substudy, after an average follow‑up of 7.1 years, daily CE-alone was not associated with an increased risk of invasive breast cancer [relative risk (RR) 0.80] compared to placebo^6 [see Clinical Studies (14.5)].

Consistent with the WHI clinical trials, observational studies have also reported an increased risk of breast cancer with estrogen plus progestin therapy, and a smaller increase in the risk for breast cancer with estrogen-alone therapy, after several years of use. One large meta-analysis of prospective cohort studies reported increased risks that were dependent upon duration of use and could last up to >10 years after discontinuation of estrogen plus progestin therapy and estrogen-alone therapy. Extension of the WHI Trials also demonstrated increased breast cancer risk associated with estrogen plus progestin therapy. Observational studies also suggest that the risk of breast cancer was greater, and became apparent earlier, with estrogen plus progestin therapy as compared to estrogen-alone therapy. These studies have not generally found significant variation in the risk of breast cancer among different estrogen plus progestin combinations, doses, or routes of administration.

The use of estrogen-alone and estrogen plus progestin therapy has been reported to result in an increase in abnormal mammograms requiring further evaluation.

In a one-year trial among 1,176 women who received either unopposed 1 mg estradiol or a combination of 1 mg estradiol plus one of three different doses of NETA (0.1, 0.25, 0.5 mg), seven new cases of breast cancer were diagnosed, two of which occurred among the group of 295 women treated with Lopreeza 1 mg/0.5 mg and two of which occurred among the group of 294 women treated with 1 mg estradiol/0.1 mg NETA.

All women should receive yearly breast examinations by a healthcare provider and perform monthly breast self-examinations. In addition, mammography examinations should be scheduled based on patient age, risk factors, and prior mammogram results.

Endometrial Cancer

An increased risk of endometrial cancer has been reported with the use of unopposed estrogen therapy in a woman with a uterus. The reported endometrial cancer risk among unopposed estrogen users is about 2- to 12-fold greater than in nonusers, and appears dependent on duration of treatment and on estrogen dose. Most studies show no significant increased risk associated with use of estrogens for less than 1 year. The greatest risk appears to be associated with prolonged use, with increased risks of 15- to 24‑fold for 5 to 10 years or more. This risk has been shown to persist for at least 8 to 15 years after estrogen therapy is discontinued.

Clinical surveillance of all women using estrogen-alone or estrogen plus progestogen therapy is important. Perform adequate diagnostic measures, including directed or random endometrial sampling when indicated, to rule out malignancy in postmenopausal women with undiagnosed persistent or recurring abnormal genital bleeding with unknown etiology.

There is no evidence that the use of natural estrogens results in a different endometrial risk profile than synthetic estrogens of equivalent estrogen dose. Adding a progestogen to estrogen therapy in postmenopausal women has been shown to reduce the risk of endometrial hyperplasia, which may be a precursor to endometrial cancer.

Endometrial hyperplasia occured at a rate of approximately 1 percent or less with Lopreeza in a clinical trial.

Ovarian Cancer

The CE plus MPA substudy of WHI reported that estrogen plus progestin increased the risk of ovarian cancer. After an average follow-up of 5.6 years, the relative risk for ovarian cancer for CE plus MPA versus placebo was 1.58 (95 percent confidence interval [CI], 0.77-3.24), but it was not statistically significant. The absolute risk for CE plus MPA versus placebo was 4 versus 3 cases per 10,000 women-years.^7

A meta-analysis of 17 prospective and 35 retrospective epidemiology studies found that women who used hormonal therapy for menopausal symptoms had an increased risk for ovarian cancer. The primary analysis, using case-control comparisons, included 12,110 cancer cases from the 17 prospective studies. The relative risks associated with current use of hormonal therapy was 1.41 (95% CI 1.32 to 1.50); there was no difference in the risk estimates by duration of the exposure (less than 5 years [median of 3 years] vs. greater than 5 years [median of 10 years] of use before the cancer diagnosis). The relative risk associated with combined current and recent use (discontinued use within 5 years before cancer diagnosis) was 1.37 (95% CI 1.27-1.48), and the elevated risk was significant for both estrogen-alone and estrogen plus progestin products. The exact duration of hormone therapy use associated with an increased risk of ovarian cancer, however, is unknown.

5.3 Probable Dementia

In the WHI Memory Study (WHIMS) estrogen plus progestin ancillary study, a population of 4,532 postmenopausal women 65 to 79 years of age was randomized to daily CE (0.625 mg) plus MPA (2.5 mg) or placebo.

After an average follow-up of 4 years, 40 women in the CE plus MPA group and 21 women in the placebo group were diagnosed with probable dementia. The relative risk of probable dementia for the CE plus MPA versus placebo was 2.05 (95 percent CI, 1.21-3.48). The absolute risk of probable dementia for CE plus MPA versus placebo was 45 versus 22 cases per 10,000 women-years ^8 [see Use in Specific Populations (8.5), and Clinical Studies (14.6)].

In the WHIMS estrogen-alone ancillary study, a population of 2,947 hysterectomized women 65 to 79 years of age was randomized to daily CE (0.625 mg)-alone or placebo. After an average follow-up of 5.2 years, 28 women in the estrogen-alone group and 19 women in the placebo group were diagnosed with probable dementia. The relative risk of probable dementia for CE-alone versus placebo was 1.49 (95 percent CI, 0.83-2.66). The absolute risk of probable dementia for CE-alone versus placebo was 37 versus 25 cases per 10,000 women-years ^8 [see Use in Specific Populations (8.5), and Clinical Studies (14.6)].

When data from the two populations in the WHIMS estrogen-alone and estrogen plus progestin ancillary studies were pooled as planned in the WHIMS protocol, the reported overall relative risk of probable dementia was 1.76 (95 percent CI, 1.19-2.60). Since both ancillary studies were conducted in women 65 to 79 years of age, it is unknown whether these findings apply to younger postmenopausal women^8 [see Use in Specific Populations (8.5), and Clinical Studies (14.6)].

5.4 Gallbladder Disease

A 2- to 4-fold increase in the risk of gallbladder disease requiring surgery in postmenopausal women receiving estrogens has been reported.

5.5 Hypercalcemia

Estrogen administration may lead to severe hypercalcemia in women with breast cancer and bone metastases. Discontinue estrogens, including Lopreeza if hypercalcemia occurs, and take appropriate measures to reduce the serum calcium level.

5.6 Vision Abnormalities

Retinal vascular thrombosis has been reported in women receiving estrogens. Discontinue Lopreeza pending examination if there is a sudden partial or complete loss of vision, or a sudden onset of proptosis, diplopia, or migraine. Permanently discontinue estrogens, including Lopreeza, if examination reveals papilledema or retinal vascular lesions.

5.7 Addition of a Progestogen When a Woman Has Not Had a Hysterectomy

Studies of the addition of a progestogen for 10 or more days of a cycle of estrogen administration, or daily with estrogen in a continuous regimen, have reported a lowered incidence of endometrial hyperplasia than would be induced by estrogen treatment alone. Endometrial hyperplasia may be a precursor to endometrial cancer.

There are, however, possible risks that may be associated with the use of progestogens with estrogens compared to estrogen-alone regimens. These include an increased risk of breast cancer.

5.8 Elevated Blood Pressure

In a small number of case reports, substantial increases in blood pressure have been attributed to idiosyncratic reactions to estrogens. In a large, randomized, placebo-controlled clinical trial, a generalized effect of estrogen therapy on blood pressure was not seen.

5.9 Exacerbation of Hypertriglyceridemia

In women with pre-existing hypertriglyceridemia, estrogen therapy may be associated with elevations of plasma triglycerides leading to pancreatitis. Discontinue Lopreeza if pancreatitis occurs.

5.10 Hepatic Impairment and/or Past History of Cholestatic Jaundice

Estrogens may be poorly metabolized in women with hepatic impairment. Exercise caution in any woman with a history of cholestatic jaundice associated with past estrogen use or with pregnancy. In the case of recurrence of cholestatic jaundice, discontinue Lopreeza.

5.11 Exacerbation of Hypothyroidism

Estrogen administration leads to increased thyroid-binding globulin (TBG) levels. Women with normal thyroid function can compensate for the increased TBG by making more thyroid hormone, thus maintaining free T4 and T3 serum concentrations in the normal range. Women dependent on thyroid hormone replacement therapy who are also receiving estrogen may require increased doses of their thyroid replacement therapy. Monitor thyroid function in these women during treatment with Lopreeza to maintain their free thyroid hormone levels in an acceptable range.

5.12 Fluid Retention

Estrogens plus progestogens may cause some degree of fluid retention. Monitor any woman with a condition(s) that might predispose her to fluid retention, such as a cardiac or renal impairment. Discontinue estrogen plus progestogen therapy, including Lopreeza, with evidence of medically concerning fluid retention.

5.13 Hypocalcemia

Estrogen-induced hypocalcemia may occur in women with hypoparathyroidism. Consider whether the benefits of estrogen therapy, including Lopreeza, outweigh the risks in such women.

5.14 Exacerbation of Endometriosis

A few cases of malignant transformation of residual endometrial implants have been reported in women treated post-hysterectomy with estrogen-alone therapy.

5.15 Hereditary Angioedema

Exogenous estrogens may exacerbate symptoms of angioedema in women with hereditary angioedema. Consider whether the benefits of estrogen therapy, including Lopreeza, outweigh the risks in such women.

5.16 Exacerbation of Other Conditions

Estrogen therapy, including Lopreeza, may cause an exacerbation of asthma, diabetes mellitus, epilepsy, migraine, porphyria, systemic lupus erythematosus, and hepatic hemangiomas. Consider whether the benefits of estrogen therapy outweigh the risks in such women.

5.17 Laboratory Tests

Serum follicle stimulating hormone (FSH) and estradiol levels have not been shown to be useful in the management of moderate to severe vasomotor symptoms and moderate to severe symptoms of vulvar and vaginal atrophy.

5.18 Drug-Laboratory Test Interactions

- Accelerated prothrombin time, partial thromboplastin time, and platelet aggregation time; increased platelet count; increased factors II, VII antigen, VIII coagulant activity, IX, X, XII, VII-X complex, and beta-thromboglobulin; decreased levels of anti-factor Xa and antithrombin III, decreased antithrombin III activity, increased levels of fibrinogen and fibrinogen activity; increased plasminogen antigen and activity.
- Increased thyroid-binding globulin (TBG) levels leading to increased circulating total thyroid hormone levels as measured by protein-bound iodine (PBI), T4 levels (by column or by radioimmunoassay), or T3 levels by radioimmunoassay. T3 resin uptake is decreased, reflecting the elevated TBG. Free T4 and free T3 concentrations are unaltered. Women on thyroid replacement therapy may require higher doses of thyroid hormone.
- Other binding proteins may be elevated in serum, for example, corticosteroid binding globulin (CBG), sex hormone-binding globulin (SHBG), leading to increased total circulating corticosteroids and sex steroids, respectively. Free hormone concentrations, such as testosterone and estradiol, may be decreased. Other plasma proteins may be increased (angiotensinogen/rennin substrate, alpha-1 antitrypsin, ceruloplasmin).
- Increased plasma high-density lipoprotein (HDL) and HDL2 cholesterol subfraction concentration, reduced low-density lipoprotein (LDL) cholesterol concentration, increased triglyceride levels.

- Impaired glucose tolerance.

6 ADVERSE REACTIONS

The following serious adverse reactions are discussed elsewhere in the labeling:

- Cardiovascular Disorders [see Boxed Warning, Warnings and Precautions (5.1)]
- Malignant Neoplasms [see Boxed Warning, Warnings and Precautions (5.2)]

6.1 Clinical Trials Experience

Because clinical trials are conducted under widely varying conditions, adverse reaction rates observed in the clinical trials of a drug cannot be directly compared to rates in the clinical trials of another drug and may not reflect the rates observed in practice.

Adverse reactions reported with Lopreeza 1 mg/0.5 mg by investigators during clinical trials regardless of causality assessment are shown in Table 1.

TABLE 1

ALL TREATMENT-EMERGENT ADVERSE REACTIONS REGARDLESS OF RELATIONSHIP REPORTED AT A FREQUENCY OF ≥ 5 PERCENT WITH LOPREEZA 1 MG/0.5 MG

 | Endometrial; Hyperplasia Study | (12-Months) | Vasomotor; Symptoms Study | (3-Months) | Osteoporosis; Study | (2-Years)
 | Lopreeza; 1 mg/0.5 mg | 1 mg E2 | Lopreeza; 1 mg/0.5 mg | Placebo | Lopreeza; 1 mg/0.5 mg | Placebo
 | (n=295) | (n=296) | (n=29) | (n=34) | (n=47) | (n=48)
Body as a Whole
Back Pain | 6% | 5% | 3% | 3% | 6% | 4%
Headache | 16% | 16% | 17% | 18% | 11% | 6%
Digestive System
Nausea | 3% | 5% | 10% | 0% | 11% | 0%
Gastroenteritis | 2% | 2% | 0% | 0% | 6% | 4%
Nervous System
Insomnia | 6% | 4% | 3% | 3% | 0% | 8%
Emotional Lability | 1% | 1% | 0% | 0% | 6% | 0%
Respiratory System
Upper Respiratory; Tract Infection | 18% | 15% | 10% | 6% | 15% | 19%
Sinusitis | 7% | 11% | 7% | 0% | 15% | 10%
Metabolic and Nutritional
Weight Increase | 0% | 0% | 0% | 0% | 9% | 6%
Urogenital System
Breast Pain | 24% | 10% | 21% | 0% | 17% | 8%
Post-Menopausal Bleeding | 5% | 15% | 10% | 3% | 11% | 0%
Uterine Fibroid | 5% | 4% | 0% | 0% | 4% | 8%
Ovarian Cyst | 3% | 2% | 7% | 0% | 0% | 8%
Resistance Mechanism
Infection Viral | 4% | 6% | 0% | 3% | 6% | 6%
Moniliasis Genital | 4% | 7% | 0% | 0% | 6% | 0%
Secondary Terms
Injury Accidental | 4% | 3% | 3% | 0% | 17%* | 4%*
Other Events | 2% | 3% | 3% | 0% | 6% | 4%

* including one upper extremity fracture in each group

Adverse reactions reported with Lopreeza 0.5 mg/0.1 mg by investigators during clinical trials regardless of causality assessment are shown in Table 2.

TABLE 2

ALL TREATMENT-EMERGENT ADVERSE REACTIONS REGARDLESS OF RELATIONSHIP REPORTED AT A FREQUENCY OF ≥ 5 PERCENT WITH LOPREEZA 0.5 MG/0.1 MG

 | Lopreeza; 0.5 mg/0.1 mg | Placebo
 | (n=194) | (n=200)
Body as a Whole
Back Pain | 10% | 4%
Headache | 22% | 19%
Pain in extremity | 5% | 4%
Digestive System
Nausea | 5% | 4%
Diarrhea | 6% | 6%
Respiratory System
Nasopharyngitis | 21% | 18%
Urogenital System
Endometrial thickening | 10% | 4%
Vaginal hemorrhage | 26% | 12%

6.2 Postmarketing Experience

The following adverse reactions have been identified during post-approval use of Lopreeza. Because these reactions are reported voluntarily from a population of uncertain size, it is not always possible to reliably estimate their frequency or establish a causal relationship to drug exposure.

Genitourinary System

Changes in vaginal bleeding pattern and abnormal withdrawal bleeding or flow; breakthrough bleeding; spotting; dysmenorrhea, increase in size of uterine leiomyomata; vaginitis, including vaginal candidiasis; change in amount of cervical secretion; changes in cervical ectropion; pre-menstrual-like syndrome; cystitis-like syndrome; ovarian cancer; endometrial hyperplasia; endometrial cancer.

Breast

Tenderness, enlargement, pain, nipple discharge, galactorrhea; fibrocystic breast changes; breast cancer.

Cardiovascular

Deep and superficial venous thrombosis; pulmonary embolism; thrombophlebitis; myocardial infarction, stroke; increase in blood pressure.

Gastrointestinal

Nausea, vomiting; changes in appetite; cholestatic jaundice; abdominal pain/cramps, flatulence, bloating; increased incidence of gallbladder disease and pancreatitis.

Skin

Chloasma or melasma that may persist when drug is discontinued; erythema multiforme; erythema nodosum; hemorrhagic eruption; loss of scalp hair; seborrhea; hirsutism; itching; skin rash; pruritus.

Eyes

Retinal vascular thrombosis, intolerance to contact lenses.

Central Nervous System

Headache; migraine; dizziness; mental depression; chorea; insomnia; nervousness; mood disturbances; irritability; exacerbation of epilepsy; dementia.

Miscellaneous

Increase or decrease in weight; edema; leg cramps; changes in libido; fatigue; exacerbation of asthma; increased triglycerides; hypersensitivity; anaphylactoid/anaphylactic reactions.

7 DRUG INTERACTIONS

Co-administration of estradiol with norethindrone acetate did not elicit any apparent influence on the pharmacokinetics of norethindrone acetate. Similarly, no relevant interaction of norethindrone acetate on the pharmacokinetics of estradiol was found within the NETA dose range investigated in a single dose study.

Estradiol

In-vitro and in-vivo studies have shown that estrogens are metabolized partially by cytochrome P450 3A4 (CYP3A4). Therefore, inducers or inhibitors of CYP3A4 may affect estrogen drug metabolism. Inducers of CYP3A4 such as St. John’s wort (Hypericum perforatum) preparations, phenobarbital, carbamazepine, and rifampin may reduce plasma concentrations of estrogens, possibly resulting in a decrease in therapeutic effects and/or changes in the uterine bleeding profile. Inhibitors of CYP3A4 such as erythromycin, clarithromycin, ketoconazole, itraconazole, ritonavir and grapefruit juice may increase plasma concentrations of estrogens and result in adverse reactions.

Norethindrone Acetate

Drugs or herbal products that induce or inhibit cytochrome P-450 enzymes, including CYP3A4, may decrease or increase the serum concentrations of norethindrone.

8 USE IN SPECIFIC POPULATIONS

8.1 Pregnancy

Risk Summary

Lopreeza is not indicated for use in pregnancy. There are no data with the use of Lopreeza in pregnant women; however, epidemiologic studies and meta-analyses have not found an increased risk of genital or nongenital birth defects (including cardiac anomalities and limb-reduction defects) following exposure to combined hormonal contraceptives (estrogen and progestins) before conception or during early pregnancy.

In the U.S. general population, the estimated background risk of major birth defects and miscarriage in clinically recognized pregnancies is 2% to 4% and 15% to 20%, respectively.

8.2 Lactation

Risk Summary

Estrogens plus progestogens are present in human milk and can reduce milk production in breast-feeding women. This reduction can occur at any time but is less likely to occur once breast-feeding is well established. The developmental and health benefits of breastfeeding should be considered along with the mother’s clinical need for Lopreeza and any potential adverse effects on the breastfed child from Lopreeza or from the underlying maternal condition.

8.4 Pediatric Use

Lopreeza is not indicated for use in pediatric patients. Clinical studies have not been conducted in the pediatric population.

8.5 Geriatric Use

There have not been sufficient numbers of geriatric women involved in clinical studies utilizing Lopreeza to determine whether those over 65 years of age differ from younger subjects in their response to Lopreeza.

The Women’s Health Initiative Studies

In the WHI estrogen plus progestin substudy (daily CE [0.625 mg] plus MPA [2.5 mg] versus placebo), there was a higher relative risk of nonfatal stroke and invasive breast cancer in women greater than 65 years of age [see Clinical Studies (14.5)].

In the WHI estrogen-alone substudy (daily CE [0.625 mg]-alone versus placebo), there was a higher relative risk of stroke in women greater than 65 years of age [see Clinical Studies (14.5)].

The Women’s Health Initiative Memory Study

In the WHIMS ancillary studies of postmenopausal women 65 to 79 years of age, there was an increased risk of developing probable dementia in women receiving estrogen plus progestin or estrogen-alone when compared to placebo. It is unknown whether this finding applies to younger postmenopausal women [see Warnings and Precautions (5.3), and Clinical Studies (14.6)].

Since both ancillary studies were conducted in women 65 to 79 years of age, it is unknown whether these findings apply to younger postmenopausal women^8 [see Warnings and Precautions (5.3), and Clinical Studies (14.6)].

10 OVERDOSAGE

Overdosage of estrogen plus progestogen may cause nausea, vomiting, breast tenderness, abdominal pain, drowsiness and fatigue, and withdrawal bleeding may occur in women. Treatment of overdose consists of discontinuation of Lopreeza therapy with institution of appropriate symptomatic care.

11 DESCRIPTION

Lopreeza 1 mg/0.5 mg is a single tablet for oral administration containing 1 mg of estradiol and 0.5 mg of norethindrone acetate and the following excipients: lactose monohydrate, starch (corn), copovidone, talc, magnesium stearate, hypromellose and triacetin.

Lopreeza 0.5 mg/0.1 mg is a single tablet for oral administration containing 0.5 mg of estradiol and 0.1 mg of norethindrone acetate and the following excipients: lactose monohydrate, starch (corn), hydroxypropylcellulose, talc, magnesium stearate, hypromellose and triacetin.

Estradiol is a white or almost white crystalline powder. Its chemical name is estra-1, 3, 5 (10)-triene-3, 17β-diol hemihydrate with the empirical formula of C18H24O2,1/2 H2O and a molecular weight of 281.4. The structural formula of E2 is as follows:

Estradiol

Norethindrone acetate (NETA) is a white or yellowish-white crystalline powder. Its chemical name is 17β -acetoxy-19-nor-17α -pregn-4-en-20-yn-3-one with the empirical formula of C22H28O3 and molecular weight of 340.5. The structural formula of NETA is as follows:

Norethindrone Acetate

12 CLINICAL PHARMACOLOGY

12.1 Mechanism of Action

Endogenous estrogens are largely responsible for the development and maintenance of the female reproductive system and secondary sexual characteristics. Although circulating estrogens exist in a dynamic equilibrium of metabolic interconversions, estradiol is the principal intracellular human estrogen and is substantially more potent than its metabolites, estrone and estriol, at the receptor level.

The primary source of estrogen in normally cycling adult women is the ovarian follicle, which secretes 70 to 500 mcg of estradiol daily, depending on the phase of the menstrual cycle. After menopause, most endogenous estrogen is produced by conversion of androstenedione, secreted by the adrenal cortex, to estrone in the peripheral tissues. Thus, estrone and the sulfate-conjugated form, estrone sulfate, are the most abundant circulating estrogens in postmenopausal women.

Estrogens act through binding to nuclear receptors in estrogen-responsive tissues. To date, two estrogen receptors have been identified. These vary in proportion from tissue to tissue.

Circulating estrogens modulate the pituitary secretion of the gonadotropins, luteinizing hormone (LH), and FSH through a negative feedback mechanism. Estrogens act to reduce the elevated levels of these hormones seen in postmenopausal women.

Progestin compounds enhance cellular differentiation and generally oppose the actions of estrogens by decreasing estrogen receptor levels, increasing local metabolism of estrogens to less active metabolites, or inducing gene products that blunt cellular responses to estrogen. Progestins exert their effects in target cells by binding to specific progesterone receptors that interact with progesterone response elements in target genes. Progesterone receptors have been identified in the female reproductive tract, breast, pituitary, hypothalamus, and central nervous system.

12.2 Pharmacodynamics

Generally, a serum estrogen concentration does not predict an individual woman’s therapeutic response to Lopreeza nor her risk for adverse outcomes. Likewise, exposure comparisions across different estrogen products to infer efficacy or safety for the individual woman may not be valid.

12.3 Pharmacokinetics

Absorption

Estradiol

Estradiol is absorbed through the gastrointestinal tract. Following oral administration of Lopreeza tablets, peak plasma estradiol concentrations are reached within 5 to 8 hours. The oral bioavailability of estradiol following administration of Lopreeza 1 mg/0.5 mg when compared to a combination oral solution is 53%. Administration of Lopreeza 1 mg/0.5 mg with food did not modify the bioavailability of estradiol.

Norethindrone Acetate

After oral administration, norethindrone acetate is absorbed and transformed to norethindrone. Norethindrone reaches a peak plasma concentration within 0.5 to 1.5 hours after the administration of Lopreeza tablets. The oral bioavailability of norethindrone following administration of Lopreeza 1 mg/0.5 mg when compared to a combination oral solution is 100%. Administration of Lopreeza 1 mg/0.5 mg with food increases norethindrone AUC0-72 by 19% and decreases Cmax by 36%.

The pharmacokinetic parameters of estradiol (E2), estrone (E1), and norethindrone (NET) following oral administration of 1 Lopreeza 1 mg/0.5 mg or 2 Lopreeza 0.5 mg/0.1 mg tablet(s) to healthy postmenopausal women are summarized in Table 3.

TABLE 3

PHARMACOKINETIC PARAMETERS AFTER ADMINISTRATION OF

1 TABLET OF LOPREEZA 1 MG/0.5 MG OR 2 TABLETS OF LOPREEZA 0.5 MG/0.1 MG

TO HEALTHY POSTMENOPAUSAL WOMEN

 | 1 x Lopreeza; 1 mg/0.5 mg; (n=24) | 2 x Lopreeza; 0.5 mg/0.1 mg; (n=24)
 | Meana (%CV)b | Meana (%CV)b
Estradiolc (E2)
AUC0-t (pg/mL*h) | 766.5 (48) | 697.3 (53)
Cmax (pg/mL) | 26.8 (36) | 26.5 (37)
tmax(h): median (range) | 6.0 (0.5-16.0) | 6.5 (0.5-16.0)
t1/2(h)d | 14.0e (29) | 14.5f (27)
Estronec (E1)
AUC0-t (pg/mL*h) | 4469.1 (48) | 4506.4 (44)
Cmax (pg/mL) | 195.5 (37) | 199.5 (30)
tmax(h): median (range) | 6.0 (1.0-9.0) | 6.0 (2.0-9.0)
t1/2(h)d | 10.7 (44)g | 11.8 (25)g
Norethindrone (NET)
AUC0-t (pg/mL*h) | 21043 (41) | 8407.2 (43)
Cmax (pg/mL) | 5249.5 (47) | 2375.4 (41)
tmax(h) : median (range) | 0.7 (0.7-1.25) | 0.8 (0.7-1.3)
t1/2(h) | 9.8 (32)h | 11.4 (36)i

AUC = area under the curve, 0 – last quantifiable sample

Cmax = maximum plasma concentration,

tmax = time at maximum plasma concentration,

t1/2 = half-life,

a geometric mean; b geometric % coefficient of variation; c baseline unadjusted data; d baseline unadjusted data; e n=18; f n=16;

g n=13; h n=22; i n=21

Following continuous dosing with once-daily administration of Lopreeza 1 mg/0.5 mg, serum concentrations of estradiol, estrone, and norethindrone reached steady-state within two weeks with an accumulation of 33 to 47% above concentrations following single dose administration. Unadjusted circulating concentrations of E2, E1, and NET during Lopreeza 1 mg/0.5 mg treatment at steady-state (dosing at time 0) are provided in Figures 1a and 1b.

Figure 1a: Mean Baseline-Uncorrected Estradiol and Estrone Serum Concentration-Time Profiles Following Multiple Doses of Lopreeza 1 mg/0.5 mg (N=24)

Figure 1b: Mean Baseline-Uncorrected Norethindrone Serum Concentration-Time Profile Following Multiple Doses of Lopreeza 1 mg/0.5 mg (N=24)

Distribution

Estradiol

The distribution of exogenous estrogens is similar to that of endogenous estrogens. Estrogens are widely distributed in the body and are generally found in higher concentrations in the sex hormone target organs. Estradiol circulates in the blood bound to SHBG (37%) and to albumin (61%), while only approximately 1 to 2% is unbound.

Norethindrone Acetate

Norethindrone also binds to a similar extent to SHBG (36%) and to albumin (61%).

Metabolism

Estradiol

Exogenous estrogens are metabolized in the same manner as endogenous estrogens. Circulating estrogens exist in a dynamic equilibrium of metabolic interconversions. These transformations take place mainly in the liver. Estradiol is converted reversibly to estrone, and both can be converted to estriol, which is a major urinary metabolite. Estrogens also undergo enterohepatic recirculation via sulfate and glucuronide conjugation in the liver, biliary secretion of conjugates into the intestine, and hydrolysis in the intestine followed by reabsorption. In postmenopausal women, a significant proportion of the circulating estrogens exist as sulfate conjugates, especially estrone sulfate, which serves as a circulating reservoir for the formation of more active estrogens.

Norethindrone Acetate

The most important metabolites of norethindrone are isomers of 5α-dihydro-norethindrone and tetrahydro-norethindrone, which are excreted mainly in the urine as sulfate or glucuronide conjugates.

Excretion

Estradiol

Estradiol, estrone, and estriol are excreted in the urine along with glucuronide and sulfate conjugates. The half-life of estradiol following single dose administration of Lopreeza 1 mg/0.5 mg is 12 to 14 hours.

Norethindrone Acetate

The terminal half-life of norethindrone is about 8 to 11 hours.

13 NONCLINICAL TOXICOLOGY

13.1 Carcinogenesis, Mutagenesis, Impairment of Fertility

Long-term continuous administration of natural and synthetic estrogens in certain animal species increases the frequency of carcinomas of the breast, uterus, cervix, vagina, testis, and liver.

14 CLINICAL STUDIES

14.1 Effects on Vasomotor Symptoms in Postmenopausal Women

In a 12-week randomized clinical trial involving 92 subjects, Lopreeza 1 mg/0.5 mg was compared to 1 mg of estradiol and to placebo. The mean number and intensity of hot flushes were significantly reduced from baseline to week 4 and 12 in both the Lopreeza 1 mg/0.5 mg and the 1 mg estradiol group compared to placebo (see Figure 2).

Figure 2

Mean Weekly Number of Moderate and Severe Hot
Flushes in a 12-Week Study

In a study conducted in Europe a total of 577 postmenopausal women were randomly assigned to either Lopreeza 0.5 mg/0.1 mg, 0.5 mg E2/0.25 mg NETA, or placebo for 24 weeks of treatment. The mean number and severity of hot flushes were significantly reduced at week 4 and week 12 in the Lopreeza 0.5 mg/0.1 mg (see Figure 3) and 0.5 mg E2/0.25 mg NETA groups compared to placebo.

Figure 3

Mean Number of Moderate to Severe Hot

Flushes for Weeks 0 Through 12

14.2 Effects on the Endometrium in Postmenopausal Women

Lopreeza 1 mg/0.5 mg reduced the incidence of estrogen-induced endometrial hyperplasia at 1 year in a randomized, controlled clinical trial. This trial enrolled 1,176 postmenopausal women who were randomized to one of 4 arms: 1 mg estradiol unopposed (n=296), 1 mg E2 + 0.1 mg NETA (n=294), 1 mg E2 + 0.25 mg NETA (n=291), and Lopreeza 1 mg/0.5 mg (n=295). At the end of the study, endometrial biopsy results were available for 988 women. The results of the 1 mg estradiol unopposed arm compared to Lopreeza 1 mg/0.5 mg are shown in Table 4.

TABLE 4

INCIDENCE OF ENDOMETRIAL HYPERPLASIA WITH UNOPPOSED ESTRADIOL AND LOPREEZA 1 MG/0.5 MG IN A 12-MONTH STUDY

 | 1 mg E2 (n=296) | Lopreeza; 1 mg E2/0.5 mg NETA (n=295) | 1 mg E2/0.25 mg NETA (n=291) | 1 mg E2/0.1 mg NETA (n=294)
No. of subjects with histological evaluation at the end of the study | 247 | 241 | 251 | 249
No. (%) of subjects with endometrial hyperplasia at the end of the study | 36 (14.6%) | 1 (0.4%) | 1 (0.4%) | 2 (0.8%)

14.3 Effects on Uterine Bleeding or Spotting in Postmenopausal Women

During the initial months of therapy, irregular bleeding or spotting occurred with Lopreeza 1 mg/0.5 mg treatment. However, bleeding tended to decrease over time, and after 12 months of treatment with Lopreeza 1 mg/0.5 mg, about 86 percent of women were amenorrheic (see Figure 4).

Figure 4

Patients Treated with Lopreeza 1 mg/0.5 mg with Cumulative Amenorrhea over Time

Percentage of Women with no Bleeding or Spotting at any Cycle Through Cycle 13

Intent to Treat Population, LOCF

Note: the percentage of patients who were amenorrheic in a given cycle and through cycle 13 is shown. If data were missing, the bleeding value from the last reported day was carried forward (LOCF).

In the clinical trial with Lopreeza 0.5 mg/0.1 mg, 88 percent of women were amenorrheic after 6 months of treatment (See Figure 5).

Figure 5

Patients Treated with Lopreeza 0.5 mg/0.1 mg with

Cumulative Amenorrhea over Time

Percentage of Women with no Bleeding or Spotting at any

Cycle Through Cycle 6, Intent to Treat Population, LOCF

14.4 Effects on Bone Mineral Density in Postmenopausal Women

The results of two randomized, multicenter, calcium-supplemented (500 to 1,000 mg per day), placebo-controlled, 2 year clinical trials have shown that Lopreeza 1 mg/0.5 mg and estradiol 0.5 mg are effective in preventing bone loss in postmenopausal women. A total of 462 postmenopausal women with intact uteri and baseline BMD values for lumbar spine within 2 standard deviations of the mean in healthy young women (T-score > -2.0) were enrolled. In a US trial, 327 postmenopausal women (mean time from menopause 2.5 to 3.1 years) with a mean age of 53 years were randomized to 7 groups (0.25 mg, 0.5 mg, and 1 mg of estradiol alone, 1 mg estradiol with 0.25 mg norethindrone acetate, 1 mg estradiol with 0.5 mg norethindrone acetate, and 2 mg estradiol with 1 mg norethindrone acetate, and placebo). In a European trial (EU trial), 135 postmenopausal women (mean time from menopause 8.4 to 9.3 years) with a mean age of 58 years were randomized to 1 mg estradiol with 0.25 mg norethindrone acetate, 1 mg estradiol with 0.5 mg norethindrone acetate, and placebo. Approximately 58 percent and 67 percent of the randomized subjects in the two clinical trials, respectively, completed the two clinical trials. BMD was measured using dual-energy x-ray absorptiometry (DXA).

A summary of the results comparing Lopreeza 1 mg/0.5 mg and estradiol 0.5 mg to placebo from the two prevention trials is shown in Table 5.

TABLE 5

PERCENTAGE CHANGE (MEAN ± SD) IN BONE MINERAL DENSITY (BMD) FOR

LOPREEZA 1 MG/0.5 MG AND 0.5 MG E2†

(Intent to Treat Analysis, Last Observation Carried Forward)

 | US Trial |  |  | EU Trial
 | Placebo (n=37) | 0.5 mg E2†; (n=31) | Lopreeza; 1 mg/0.5 mg (n=37) | Placebo; (n=40) | Lopreeza; 1 mg/0.5 mg (n=38)
Lumbar spine | -2.1 ± 2.9 | 2.3 ± 2.8 * | 3.8 ± 3.0 * | -0.9 ± 4.0 | 5.4 ± 4.8 *
Femoral neck | -2.3 ± 3.4 | 0.3 ± 2.9 ** | 1.8 ± 4.1 * | -1.0 ± 4.6 | 0.7 ± 6.1
Femoral trochanter | -2.0 ± 4.3 | 1.7 ± 4.1*** | 3.7 ± 4.3 * | 0.8 ± 6.9 | 6.3 ± 7.6 *

US= United States, EU = European

† While Lopreeza 0.5 mg/0.1 mg was not directly studied in these trials, the US trial showed that addition of NETA to estradiol enhances the effect on BMD; therefore the BMD changes expected from treatment with Lopreeza 0.5 mg/0.1 mg should be at least as great as observed with estradiol 0.5 mg.
* Significantly (p<0.001) different from placebo

** Significantly (p<0.007) different from placebo

***Significantly (p<0.002) different from placebo

The overall difference in mean percentage change in BMD at the lumbar spine in the US trial (1000 mg per day calcium) between Lopreeza 1 mg/0.5 mg and placebo was 5.9 percent and between estradiol 0.5 mg and placebo was 4.4 percent. In the European trial (500 mg per day calcium), the overall difference in mean percentage change in BMD at the lumbar spine was 6.3 percent. Lopreeza 1 mg/0.5 mg and estradiol 0.5 mg also increased BMD at the femoral neck and femoral trochanter compared to placebo. The increase in lumbar spine BMD in the US and European clinical trials for Lopreeza 1 mg/0.5 mg and estradiol 0.5 mg is displayed in Figure 6.

Figure 6

Percentage Change in Bone Mineral Density (BMD) ± SEM of the Lumbar Spine (L1-L4) for

Lopreeza 1 mg/0.5 mg and Estradiol 0.5 mg

(Intent to Treat Analysis with Last Observation Carried Forward)

14.5 Women’s Health Initiative Studies

The WHI enrolled approximately 27,000 predominantly healthy postmenopausal women in two substudies to assess the risks and benefits of daily oral CE (0.625 mg)-alone or in combination with MPA (2.5 mg) compared to placebo in the prevention of certain chronic diseases. The primary endpoint was the incidence of CHD (defined as nonfatal MI, silent MI and CHD death), with invasive breast cancer as the primary adverse outcome. A “global index” included the earliest occurrence of CHD, invasive breast cancer, stroke, PE, endometrial cancer (only in the CE plus MPA substudy), colorectal cancer, hip fracture, or death due to other cause. These substudies did not evaluate the effects of CE plus MPA or CE-alone on menopausal symptoms.

WHI Estrogen Plus Progestin Substudy

The WHI estrogen plus progestin substudy was stopped early. According to the predefined stopping rule, after an average follow-up of 5.6 years of treatment, the increased risk of invasive breast cancer and cardiovascular events exceeded the specified benefits included in the “global index.” The absolute excess risk of events included in the “global index” was 19 per 10,000 women-years.

For those outcomes included in the WHI “global index,” that reached statistical significance after 5.6 years of follow-up, the absolute excess risks per 10,000 women-years in the group treated with CE plus MPA were 7 more CHD events, 8 more strokes, 10 more PEs, and 8 more invasive breast cancers, while the absolute risk reductions per 10,000 women-years were 6 fewer colorectal cancers and 5 fewer hip fractures.

Results of the CE plus MPA substudy, which included 16,608 women (average 63 years of age, range 50 to 79; 83.9 percent White, 6.8 percent Black, 5.4 percent Hispanic, 3.9 percent Other) are presented in Table 6. These results reflect centrally adjudicated data after an average follow-up of 5.6 years.

Table 6: Relative and Absolute Risk Seen in the Estrogen Plus Progestin Substudy of WHI at an Average of 5.6 Yearsa,b

Event | Relative Risk CE/MPA versus Placebo (95% nCIc) | CE/MPA n = 8,506 | Placebo n = 8,102
 |  | Absolute Risk per 10,000 Women-Years
CHD events | 1.23 (0.99-1.53) | 41 | 34
Non-fatal MI | 1.28 (1.00-1.63) | 31 | 25
CHD death | 1.10 (0.70-1.75) | 8 | 8
All strokes | 1.31 (1.03–1.68) | 33 | 25
Ischemic stroke | 1.44 (1.09–1.90) | 26 | 18
Deep vein thrombosisd | 1.95 (1.43–2.67) | 26 | 13
Pulmonary embolism | 2.13 (1.45–3.11) | 18 | 8
Invasive breast cancere | 1.24 (1.01–1.54) | 41 | 33
Colorectal cancer | 0.61 (0.42–0.87) | 10 | 16
Endometrial cancerd | 0.81 (0.48–1.36) | 6 | 7
Cervical cancerd | 1.44 (0.47–4.42) | 2 | 1
Hip fracture | 0.67 (0.47–0.96) | 11 | 16
Vertebral fracturesd | 0.65 (0.46–0.92) | 11 | 17
Lower arm/wrist fracturesd | 0.71 (0.59–0.85) | 44 | 62
Total fracturesd | 0.76 (0.69–0.83) | 152 | 199
Overall Mortalityf | 1.00 (0.83-1.19) | 52 | 52
Global Indexg | 1.13 (1.02-1.25) | 184 | 165

a Adapted from numerous WHI publications. WHI publications can be viewed at www.nhlbi.nih.gov/whi.

b Results are based on centrally adjudicated data.

c Nominal confidence intervals unadjusted for multiple looks and multiple comparisons.

d Not included in “global index”.

eIncludes metastatic and non-metastatic breast cancer, with the exception of in situ breast cancer.

f All deaths, except from breast or colorectal cancer, definite or probable CHD, PE or cerebrovascular disease.

g A subset of the events was combined in a “global index” defined as the earliest occurrence of CHD events, invasive breast cancer, stroke, pulmonary embolism, colorectal cancer, hip fracture, or death due to other causes.

Timing of the initiation of estrogen plus progestin therapy relative to the start of menopause may affect the overall risk benefit profile. The WHI estrogen plus progestin substudy, stratified by age, showed in women 50 to 59 years of age a non-significant trend toward reduced risk for overall mortality [hazard ratio (HR) 0.69 (95 percent CI, 0.44-1.07)].

WHI Estrogen-Alone Substudy

The WHI estrogen-alone substudy was stopped early because an increased risk of stroke was observed, and it was deemed that no further information would be obtained regarding the risks and benefits of estrogen-alone in predetermined primary endpoints.

Results of the estrogen-alone substudy, which included 10,739 women (average 63 years of age, range 50 to 79; 75.3 percent White, 15.1 percent Black, 6.1 percent Hispanic, 3.6 percent Other), after an average follow-up of 7.1 years, are presented in Table 7.

Table 7: Relative and Absolute Risk Seen in the Estrogen-Alone Substudy of WHIa

Event | Relative Risk CE versus Placebo (95% nCIb) | CE n = 5,310 | Placebo n = 5,429
 |  | Absolute Risk per 10,000 Women-Years
CHD eventsc | 0.95 (0.78–1.16) | 54 | 57
Non-fatal MIc | 0.91 (0.73–1.14) | 40 | 43
CHD deathc | 1.01(0.71–1.43) | 16 | 16
All strokesc | 1.33 (1.05-1.68) | 45 | 33
Ischemic strokeb | 1.55 (1.19 – 2.01) | 38 | 25
Deep vein thrombosisc,d | 1.47 (1.06–2.06) | 23 | 15
Pulmonary embolismc | 1.37 (0.90–2.07) | 14 | 10
Invasive breast cancerc | 0.80 (0.62–1.04) | 28 | 34
Colorectal cancere | 1.08 (0.75–1.55) | 17 | 16
Hip fracturec | 0.65 (0.45–0.94) | 12 | 19
Vertebral fracturesc,d | 0.64 (0.44-0.93) | 11 | 18
Lower arm/wrist fracturesc,d | 0.58 (0.47-0.72) | 35 | 59
Total fracturesc,d | 0.71 (0.64-0.80) | 144 | 197
Death due to other causese,f | 1.08 (0.88–1.32) | 53 | 50
Overall mortalityc,d | 1.04 (0.88–1.22) | 79 | 75
Global Indexg | 1.02 (0.92–1.13) | 206 | 201

a Adapted from numerous WHI publications. WHI publications can be viewed at www.nhlbi.nih.gov/whi.

b Nominal confidence intervals unadjusted for multiple looks and multiple comparisons.

c Results are based on centrally adjudicated data for an average follow-up of 7.1 years.

d Not included in “global index”.

e Results are based on an average follow-up of 6.8 years.

f All deaths, except from breast or colorectal cancer, definite or probable CHD, PE or cerebrovascular disease.

g A subset of the events was combined in a “global index,” defined as the earliest occurrence of CHD events, invasive breast cancer, stroke, pulmonary embolism, colorectal cancer, hip fracture, or death due to other causes.

For those outcomes included in the WHI “global index” that reached statistical significance, the absolute excess risk per 10,000 women-years in the group treated with CE-alone was 12 more strokes, while the absolute risk reduction per 10,000 women-years was 7 fewer hip fractures.^9 The absolute excess risk of events included in the “global index” was a non-significant 5 events per 10,000 women-years. There was no difference between the groups in terms of all-cause mortality.

No overall difference for primary CHD events (nonfatal MI, silent MI and CHD death) and invasive breast cancer incidence in women receiving CE-alone compared with placebo was reported in final centrally adjudicated results from the estrogen-alone substudy, after an average follow up of 7.1 years.

Centrally adjudicated results for stroke events from the estrogen-alone substudy, after an average follow-up of 7.1 years, reported no significant difference in distribution of stroke subtype or severity, including fatal strokes, in women receiving CE-alone compared to placebo. Estrogen-alone increased the risk for ischemic stroke, and this excess risk was present in all subgroups of women examined.^10

Timing of the initiation of estrogen-alone therapy relative to the start of menopause may affect the overall risk benefit profile. The WHI estrogen-alone substudy, stratified by age, showed in women 50 to 59 years of age a non-significant trend toward reduced risk for CHD [HR 0.63 (95 percent CI, 0.36-1.09)] and overall mortality [HR 0.71 (95 percent CI, 0.46-1.11)].

14.6 Women’s Health Initiative Memory Study

The WHIMS estrogen plus progestin ancillary study of WHI enrolled 4,532 predominantly healthy postmenopausal women 65 years of age and older (47 percent were 65 to 69 years of age, 35 percent were 70 to 74 years of age, 18 percent were 75 years of age and older) to evaluate the effects of daily CE (0.625 mg) plus MPA (2.5 mg) on the incidence of probable dementia (primary outcome) compared to placebo.

After an average follow-up of 4 years, the relative risk of probable dementia for CE plus MPA versus placebo was 2.05 (95 percent CI, 1.21-3.48). The absolute risk of probable dementia for CE plus MPA versus placebo was 45 versus 22 cases per 10,000 women-years. Probable dementia as defined in this study included Alzheimer’s disease (AD), vascular dementia (VaD) and mixed types (having features of both AD and VaD). The most common classification of probable dementia in the treatment group and the placebo group was AD. Since the ancillary study was conducted in women 65 to 79 years of age, it is unknown whether these findings apply to younger postmenopausal women [see Warnings and Precautions (5.3), and Use in Specific Populations (8.5)].

The WHIMS estrogen-alone ancillary study of WHI study enrolled 2,947 predominantly healthy hysterectomized postmenopausal women 65 to 79 years of age (45 percent were 65 to 69 years of age, 36 percent were 70 to 74 years of age, 19 percent were 75 years of age and older) to evaluate the effects of daily CE (0.625 mg)-alone on the incidence of probable dementia (primary outcome) compared to placebo.

After an average follow-up of 5.2 years, the relative risk of probable dementia for CE-alone versus placebo was 1.49 (95 percent CI, 0.83-2.66). The absolute risk of probable dementia for CE-alone versus placebo was 37 versus 25 cases per 10,000 women-years. Probable dementia as defined in this study included AD, VaD and mixed types (having features of both AD and VaD). The most common classification of probable dementia in the treatment group and the placebo group was AD. Since the ancillary study was conducted in women 65 to 79 years of age, it is unknown whether these findings apply to younger postmenopausal women [see Warnings and Precautions (5.3), and Use in Specific Populations (8.5)].

When data from the two populations were pooled as planned in the WHIMS protocol, the reported overall relative risk for probable dementia was 1.76 (95 percent CI, 1.19-2.60). Differences between groups became apparent in the first year of treatment. It is unknown whether these findings apply to younger postmenopausal women [see Warnings and Precautions (5.3), and Use in Specific Populations (8.5)].

15 REFERENCES

1. Rossouw JE, et al. Postmenopausal Hormone Therapy and Risk of Cardiovascular Disease by Age and Years Since Menopause. JAMA. 2007;297:1465-1477.

2. Hsia J, et al. Conjugated Equine Estrogens and Coronary Heart Disease. Arch Int Med. 2006;166:357-365.

3. Cushman M, et al. Estrogen Plus Progestin and Risk of Venous Thrombosis. JAMA. 2004;292:1573-1580.

4. Curb JD, et al. Venous Thrombosis and Conjugated Equine Estrogen in Women Without a Uterus.
Arch Int Med. 2006;166:772-780.

5. Chlebowski RT, et al. Influence of Estrogen Plus Progestin on Breast Cancer and Mammography in Healthy Postmenopausal Women. JAMA. 2003;289:3234-3253.

6. Stefanick ML, et al. Effects of Conjugated Equine Estrogens on Breast Cancer and Mammography Screening in Postmenopausal Women With Hysterectomy. JAMA. 2006;295:1647-1657.

7. Anderson GL, et al. Effects of Estrogen Plus Progestin on Gynecologic Cancers and Associated Diagnostic Procedures. JAMA. 2003;290:1739-1748.

8. Shumaker SA, et al. Conjugated Equine Estrogens and Incidence of Probable Dementia and Mild Cognitive Impairment in Postmenopausal Women. JAMA. 2004;291:2947-2958.

9. Jackson RD, et al. Effects of Conjugated Equine Estrogen on Risk of Fractures and BMD in Postmenopausal Women With Hysterectomy: Results From the Women’s Health Initiative Randomized Trial. J Bone Miner Res. 2006;21:817-828.

10. Hendrix SL, et al. Effects of Conjugated Equine Estrogen on Stroke in the Women’s Health Initiative. Circulation. 2006;113:2425-2434.

16 HOW SUPPLIED/STORAGE AND HANDLING

16.1 How Supplied

Lopreeza (estradiol/norethindrone acetate) tablets, 1 mg/0.5 mgare available as white, round, biconvex, film-coated tablets, debossed with “ALH” on the one side and plain on the other side. (NDC 69238-1610-6). It is supplied as 28 tablets in a blister pack, one blister pack per carton.

Lopreeza (estradiol/norethindrone acetate) tablets, 0.5 mg/0.1 mg are available as white, round, biconvex, film-coated tablets, debossed with “ALL” on the one side and plain on the other side.

(NDC 69238-1609-6). It is supplied as 28 tablets in a blister pack, one blister pack per carton.

16.2 Storage and Handling

Store in a dry place protected from light. Store at 20° to 25°C (68° to 77°F), excursions permitted between 15° to 30°C (59° to 86°F) [see USP Controlled Room Temperature].

17 PATIENT COUNSELING INFORMATION

Advise women to read the FDA-approved patient labeling (Patient Information)

Vaginal Bleeding

Inform postmenopausal women to report any vaginal bleeding to their healthcare provider as soon as possible [see Warnings and Precautions (5.2)].

Possible Serious Adverse Reactions with Estrogen Plus Progestogen Therapy

Inform postmenopausal women of possible serious adverse reactions of estrogen plus progestogen therapy including Cardiovascular Disorders, Malignant Neoplasms, and Probable Dementia [see Warnings and Precautions (5.1, 5.2, 5.3)].

Possible Common Adverse Reactions with Estrogen Plus Progestogen Therapy

Inform postmenopausal women of possible less serious but common adverse reactions of estrogen plus progestogen therapy such as headache, breast pain and tenderness, nausea and vomiting.

Rx Only

Lopreeza® is a registered trademark of Amneal Pharmaceuticals LLC

© 2025 Amneal Pharmaceuticals LLC

Distributed by:
Amneal Pharmaceuticals LLC
Bridgewater, NJ 08807

Rev. 01-2025-03

Patient Information

Lopreeza® (lo-PREE-zuh)

(estradiol/norethindrone acetate)

tablets, for oral use

Read this Patient Information before you start using LOPREEZA and each time you get a refill. There may be new information. This information does not take the place of talking to your healthcare provider about your menopausal symptoms or your treatment.

What is the most important information I should know about LOPREEZA (a combination of estrogen and progestogen)?

- Do not use estrogens with or without progestogens to prevent heart disease, heart attacks, strokes, or dementia (decline of brain function).
- Using estrogens with progestogens may increase your chances of getting heart attacks, strokes, breast cancer, or blood clots.
- Using estrogens with progestogens may increase your chance of getting dementia, based on a study of women 65 years of age and older.
- Using estrogen-alone may increase your chance of getting cancer of the uterus (womb).
- Do not use estrogen-alone to prevent heart disease, heart attacks, strokes, or dementia (decline in brain function).
- Using estrogen-alone may increase your chances of getting strokes or blood clots.
- Using estrogen-alone may increase your chance of getting dementia, based on a study of women 65 years of age and older.
- Only one estrogen with progestogen product and dose have been shown to increase your chances of getting heart attacks, strokes, breast cancer, blood clots, and dementia. Only one estrogen-alone product and dose have been shown to increase your chances of getting strokes, blood clots, and dementia.

Because other products and doses have not been studied in the same way, it is not known how the use of LOPREEZA will affect your chances of these conditions. You and your healthcare provider should talk regularly about whether you still need treatment with LOPREEZA.

What is LOPREEZA?

LOPREEZA is a prescription medicine that contains two kinds of hormones, an estrogen and a progestogen.

What is LOPREEZA used for?

LOPREEZA is used after menopause to:

- Reduce moderate to severe hot flushes
  Estrogens are hormones made by a woman’s ovaries. The ovaries normally stop making estrogens when a woman is between 45 and 55 yrs old. This drop in body estrogen levels causes the “change of life” or menopause, the end of monthly menstrual periods. Sometimes both ovaries are removed during an operation before natural menopause takes place. The sudden drop in estrogen levels causes “surgical menopause.”
  When estrogen levels begin dropping, some women get very uncomfortable symptoms, such as feelings of warmth in the face, neck, and chest, or sudden, intense feelings of heat and sweating (“hot flashes” or “hot flushes”). In some women, the symptoms are mild, and they will not need to use estrogens. In other women, symptoms can be more severe.
- Treat moderate to severe menopausal changes in and around the vagina
  You and your healthcare provider should talk regularly about whether you still need treatment with LOPREEZA 1.0 mg/0.5 mg to treat these problems. If you use LOPREEZA 1.0 mg/0.5 mg only to treat your menopausal changes in and around your vagina, talk with your healthcare provider about whether a topical vaginal product would be better for you.
- Help reduce your chances of getting osteoporosis (thin weak bones)
  Osteoporosis from menopause is a thinning of the bones that makes them weaker and easier to break. If you use LOPREEZA to prevent osteoporosis due to menopause, talk with your healthcare provider about whether a different treatment or medicine without estrogens might be better for you.
  You and your healthcare provider should talk regularly about whether you still need treatment with LOPREEZA.
  Who should not use LOPREEZA?
  Do not use LOPREEZA if you have had your uterus (womb) removed (hysterectomy).
  LOPREEZA contains a progestogen to decrease the chance of getting cancer of the uterus. If you do not have a uterus, you do not need a progestogen and you should not us LOPREEZA.
  Do not start using LOPREEZA if you:
- have unusual vaginal bleeding
  Vaginal bleeding after menopause may be a warning sign of cancer of the uterus (womb). Your healthcare provider should check any unusual vaginal bleeding to find out the cause.
- have been diagnosed with a bleeding disorder
- currently have or have had certain cancers

Estrogens may increase the chance of getting certain types of cancers, including cancer of the breast or uterus (womb). If you have or have had cancer, talk with your healthcare provider about whether you should use LOPREEZA.

- had a stroke or heart attack
- currently have or have had blood clots
- currently have or have had liver problems
- are allergic to LOPREEZA or any of the ingredients in it.

See the list of ingredients in LOPREEZA at the end of this leaflet.

Before you use LOPREEZA, tell your healthcare provider about all of your medical conditions, including if you:

- have any unusual vaginal bleeding
  Vaginal bleeding after menopause may be a warning sign of cancer of the uterus (womb). Your healthcare provider should check any unusual vaginal bleeding to find out the cause.
- have any other medical conditions that may become worse while you are using LOPREEZA
  Your healthcare provider may need to check you more carefully if you have certain conditions, such as asthma (wheezing), epilepsy (seizures), diabetes, migraine, endometriosis, lupus, angioedema (swelling of face and tongue), problems with your heart, liver, thyroid, kidneys, or have high calcium levels in your blood.
  - are going to have surgery or will be on bed rest
    Your healthcare provider will let you know if you need to stop using LOPREEZA.
  - are pregnant or think you may be pregnant
    LOPREEZA is not for pregnant women.

- are breast feeding
  The hormones in LOPREEZA can pass into your breast milk.
  Tell your healthcare provider about all the medicines you take, including prescription and over-the-counter medicines, vitamins, and herbal supplements. Some medicines may affect how LOPREEZA works. LOPREEZA may also affect how your other medicines work. Keep a list of your medicines and show it to your healthcare provider and pharmacist when you get new medicine.
  How should I use Lopreeza?
  - Use LOPREEZA exactly as your healthcare provider tells you to use it.
  - Take 1 tablet at the same time each day.
  - You and your healthcare provider should talk regularly (every 3 to 6 months) about your dose and whether you still need treatment with LOPREEZA.
  What are the possible side effects of LOPREEZA?
  Side effects are grouped by how serious they are and how often they happen when you are treated.
  Serious, but less common side effects include:
  - heart attack
  - stroke
  - blood clots
  - breast cancer
  - cancer of the lining of the uterus (womb)
  - cancer of the ovary
  - dementia
  - high or low blood calcium levels
  - gallbladder disease
  - visual abnormalities
  - high blood pressure
  - high levels of fat (triglycerides) in your blood
  - liver problems
  - changes in your thyroid hormone levels
  - fluid retention
  - cancer changes of endometriosis
  - enlargement of benign tumors of the uterus (“fibroids”)
  - worsening swelling of face and tongue (angioedema) in women who have a history of angioedema
  - changes in laboratory tests results such as bleeding times and high blood sugar levels

Call your healthcare provider right away if you get any of the following warning signs or any other unusual symptoms that concern you:

- new breast lumps
- unusual vaginal bleeding
- changes in vision or speech
- sudden new severe headaches
- severe pains in your chest or legs with or without shortness of breath, weakness and fatigue

Common side effects of LOPREEZA include:

- irregular vaginal bleeding or spotting
- nausea
- stomach or abdominal cramps, bloating
- headache
- vomiting
- back pain
- breast pain
- diarrhea
- fluid retention
- vaginal yeast infection

These are not all the possible side effects of LOPREEZA. For more information, ask your healthcare provider or pharmacist. Tell your healthcare provider if you have any side effects that bother you or do not go away.

You may report side effects to Amneal Pharmaceuticals at 1-877-835-5472 or to FDA at 1-800-FDA-1088.

What can I do to lower my chances of a serious side effect with LOPREEZA?

- Talk with your healthcare provider regularly about whether you should continue using LOPREEZA.
- If you have a uterus, talk with your healthcare provider about whether LOPREEZA is right for you.
- In general, the addition of a progestogen is generally recommended for a woman with a uterus to reduce the chance of getting cancer of the uterus (womb).
- See your healthcare provider right away if you get vaginal bleeding while using LOPREEZA.
- Have a pelvic exam, breast exam and mammogram (breast X-ray) every year unless your healthcare provider tells you something else.

- If members of your family have had breast cancer or if you have ever had breast lumps or an abnormal mammogram (breast x-ray), you may need to have breast exams more often.

- If you have high blood pressure, high cholesterol (fat in the blood), diabetes, are overweight, or if you use tobacco, you may have higher chances for getting heart disease.
- Ask your healthcare provider for ways to lower your chances for getting heart disease.

How should I store LOPREEZA?

- Store LOPREEZA at room temperature between 68°F to 77°F (20°C to 25°C).
- Store LOPREEZA in a dry place protected from light.

KEEP LOPREEZA and all medicines out of the reach of children.

General information about the safe and effective use of LOPREEZA.

Medicines are sometimes prescribed for purposes other than those listed in Patient Information leaflets. Do not use LOPREEZA for conditions for which it was not prescribed. Do not give LOPREEZA to other people, even if they have the same symptoms you have. It may harm them.

You can ask your healthcare provider or pharmacist for information about LOPREEZA that is written for health professionals.

For more information go to www.amneal.com or call 1-877-835-5472.

What are the ingredients in LOPREEZA?

Active ingredients: estradiol and norethindrone acetate

Inactive Ingredients: lactose monohydrate, starch (corn), talc, magnesium stearate, hypromellose, and triacetin.

The 1 mg/0.5 mg tablet also contains copovidone.

The 0.5 mg/0.1 mg tablet also contains hydroxypropylcellulose.

This Patient Information has been approved by the U.S. Food and Drug Administration.

Lopreeza® is a registered trademark of Amneal Pharmaceuticals LLC.

© 2025 Amneal Pharmaceuticals LLC

Distributed by:
Amneal Pharmaceuticals LLC
Bridgewater, NJ 08807

Rev. 01-2025-03